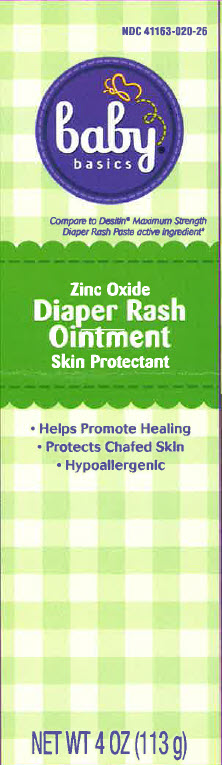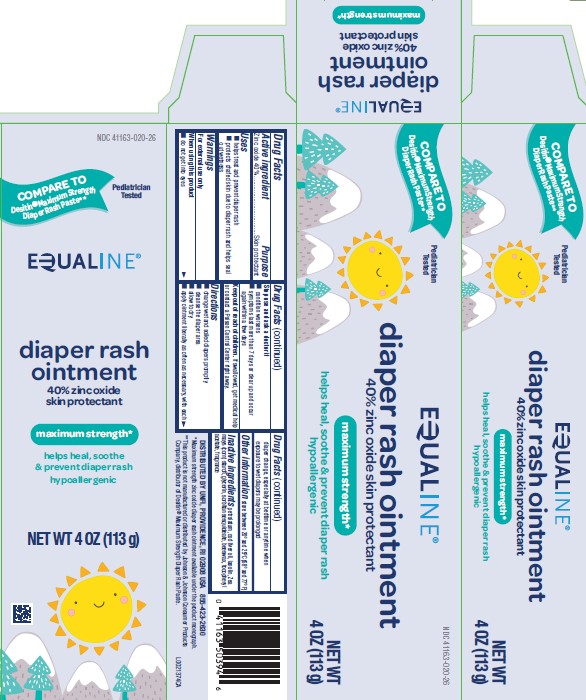 DRUG LABEL: Diaper Rash
NDC: 41163-020 | Form: OINTMENT
Manufacturer: United Natural Foods, Inc. dba UNFI
Category: otc | Type: HUMAN OTC DRUG LABEL
Date: 20260216

ACTIVE INGREDIENTS: ZINC OXIDE 400 mg/1 g
INACTIVE INGREDIENTS: STARCH, CORN; GLYCERIN; SORBITAN SESQUIOLEATE; YELLOW WAX; .ALPHA.-TOCOPHEROL ACETATE; PETROLATUM; COD LIVER OIL; LANOLIN

Baby Basics_Equaline 020.002/020AC-AD
Diaper Rash Ointment 40% Zinc Oxide

Active ingredient

Zinc oxide 40%

Purpose

Skin protectant

Uses

- helps treat and prevent diaper rash
- protects chafed skin due to diaper rash and helps seal out wetness

Warnings

For external use only

When using this product

- do not get into eyes

Stop use and ask a doctor if

- condition worsens
- symptoms last more than 7 days or clear up and occur again within a few days

Keep out of reach of children.

If swallowed, get medical help or contact a Poison Control Center right away.

Directions

- change wet and soiled diapers promptly
- cleanse the diaper area
- allow to dry
- apply ointment liberally as often as necessary, with each diaper change, especially at bedtime or anytime when exposure to wet diapers may be prolonged

Other information

store between 20⁰ and 25⁰C (68⁰ and 77⁰F)

Inactive ingredients

petrolatum, cod liver oil, lanolin, Zea mays (corn) starch, glycerin, sorbitan sesquioleate, beeswax, tocopheryl acetate, fragrance

Adverse Reactions

DISTRIBUTED BY UNFI, PROVIDENCE, RI 02908 USA

855-423-2630

Disclaimer

*Maximum strength zinc oxide diaper rash oinment available under the product monograph.

**This product is not manufactured or distributed by Johnson & Johnson Consumer Products Company, distributor of Destin®Maximum Strength Diaper Rash Paste.

Principal display panel

Baby basics

Compare to Desitin Maximum Strength Diaper Rash Paste active ingredient*

Zinc Oxide

Diaper Rash Ointment

Skin Protectant

- Helps Promote Healting
- Protects chafed skin
- Hypoallergenic

NET WT 4 OZ (113 g)

Principal display panel

NDC 41163-020-26

COMPARE TO Destin®Maximum Strength Diaper Rash Paste**

Pediatrician Tested

EQUALINE®

diaper rash ointment

40% zinc oxide

skin protectant

maximum strength*

helps heal, soothe and prevent diaper rash

hypoallergenic

NET WT 4OZ (113 g)